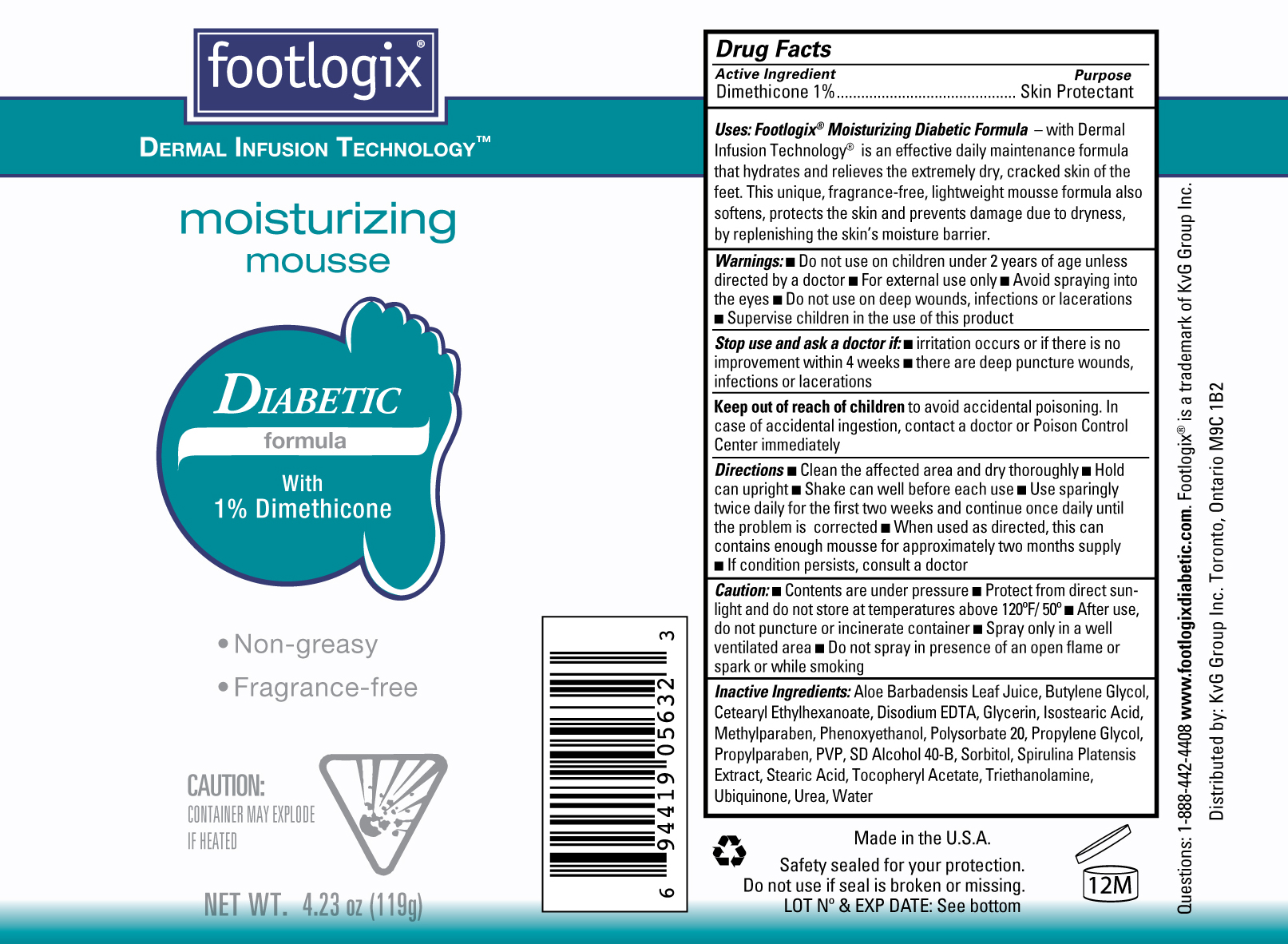 DRUG LABEL: footlogix
NDC: 42479-214 | Form: AEROSOL, FOAM
Manufacturer: KVG Group Inc 
Category: otc | Type: HUMAN OTC DRUG LABEL
Date: 20120628

ACTIVE INGREDIENTS: DIMETHICONE 1 g/100 g
INACTIVE INGREDIENTS: ALOE VERA LEAF; BUTYLENE GLYCOL; CETEARYL ETHYLHEXANOATE; EDETATE DISODIUM; GLYCERIN; ISOSTEARIC ACID; METHYLPARABEN; PHENOXYETHANOL; POLYSORBATE 20; PROPYLENE GLYCOL; PROPYLPARABEN; POVIDONE; SORBITOL; SPIRULINA PLATENSIS; STEARIC ACID; ALPHA-TOCOPHEROL ACETATE; TROLAMINE; UREA; WATER

Drug Facts

Active Ingredient

Dimethicone 1%

Purpose

Skin Protectant

INDICATIONS AND USAGE

Uses: Footlogix Moisturizing Diabetic Formula- with Dermal Infusion Technology is an effective daily maintenance formula that hydrates and relieves the extremely dry, cracked skin of the feet. This unique fragrance-free, lightweight mousse formula also softens, protects the skni and prevents damage due to dryness by replenishing the skin's moisture barrier.

WARNINGS

Warnings ■ Do not use on children 2 years of age unless directed by a doctor ■ For external use only ■ Avoid spraying into the eyes ■ Do not use on deep wounds, infections or lacerations ■ Supervise children in the use of this product

Stop use and ask a doctor if: ■ irritation occurs or if there is no improvement within 4 weeks ■ there are deep puncture wounds, infections or lacerations

Keep out of reach of children to avoid accidental poisoning. In case of accidental ingestion, contact a doctor or Poison Control Center immediately

DOSAGE AND ADMINISTRATION

Directions ■ Clean the affected area and dry thoroughly ■ Hold the can upright ■ Shake well before each use ■ Use sparingly twice daily for the first two weeks and continue once daily until the problem is corrected ■ When used as directed, this can contains enough mousse for approximately two months supply ■ If condition persists, consult a doctor

Caution: ■ Contents are under pressure ■ Protect from direct sunlight and do not store at temperatures above 120F/50C ■ After use, do not puncture or incinerate container ■ Spray only in a well ventilated area ■ Do not spray in presence of open flame or spark or while smoking

INACTIVE INGREDIENT

Inactive Ingredients Aloe Barbadensis Leaf Juice, Butylene Glycol, Cetearyl Ethylhexanoate, Disodium EDTA, Glycerin, Isostearic Acid, Methylparaben, Phenoxyethanol, Polysorbate 20, Propylene Glycol, Propylparaben, PVP, SD Alcohol 40-B, Sorbitol, Spirulina Platensis Extract, Stearic Acid, Tocopheryl Acetate, Triethanolamine, Ubiquinone, Urea, Water.

Product Label